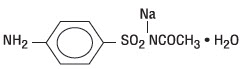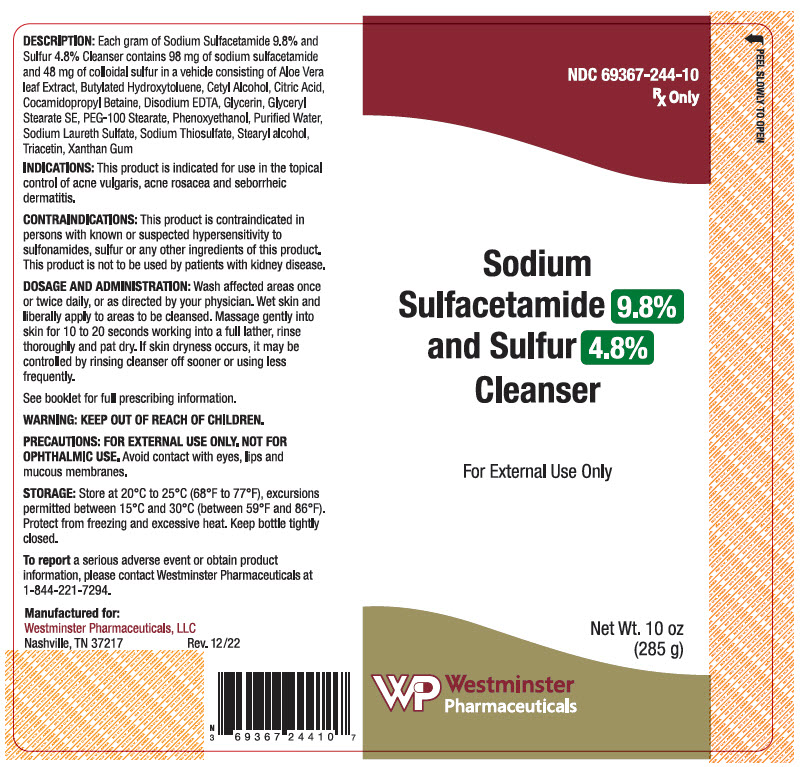 DRUG LABEL: SODIUM SULFACETAMIDE, SULFUR
NDC: 69367-244 | Form: LIQUID
Manufacturer: Westminster Pharmaceuticals, LLC
Category: prescription | Type: HUMAN PRESCRIPTION DRUG LABEL
Date: 20200521

ACTIVE INGREDIENTS: SULFACETAMIDE SODIUM 98 mg/1 g; SULFUR 48 mg/1 g
INACTIVE INGREDIENTS: BUTYLATED HYDROXYTOLUENE; CETYL ALCOHOL; COCAMIDOPROPYL BETAINE; EDETATE DISODIUM ANHYDROUS; GLYCERIN; GLYCERYL STEARATE SE; PEG-100 STEARATE; PHENOXYETHANOL; WATER; SODIUM THIOSULFATE; STEARYL ALCOHOL; TRIACETIN; XANTHAN GUM; CITRIC ACID MONOHYDRATE; SODIUM LAURETH-3 SULFATE

Sodium Sulfacetamide 9.8%
and Sulfur 4.8% Cleanser

Rx Only

FOR EXTERNAL USE ONLY. NOT FOR OPHTHALMIC USE.

DESCRIPTION

Each gram of Sodium Sulfacetamide 9.8% and Sulfur 4.8% Cleanser contains 98 mg of sodium sulfacetamide and 48 mg of colloidal sulfur in a vehicle consisting of Aloe Vera leaf Extract, Butylated Hydroxytoluene, Cetyl Alcohol, Citric Acid, Cocamidopropyl Betaine, Disodium EDTA, Glycerin, Glyceryl Stearate SE, PEG-100 Stearate, Phenoxyethanol, Puriﬁed Water, Sodium Laureth Sulfate, Sodium Thiosulfate, Stearyl alcohol, Triacetin, Xanthan Gum

Sodium sulfacetamide is a sulfonamide with antibacterial activity while sulfur acts as a keratolytic agent. Sodium sulfacetamide is C8H9N2NaO3S∙H2O with molecular weight of 254.24. Chemically sodium sulfacetamide is N-[(4-aminophenyl) sulfonyl]-acetamide, monosodium salt, monohydrate. The structural formula is:

Sodium sulfacetamide is an odorless, white, crystalline powder with a bitter taste. It is freely soluble in water, sparingly soluble in alcohol, while practically insoluble in benzene, in chloroform and in ether.

CLINICAL PHARMACOLOGY

Sodium sulfacetamide exerts a bacteriostatic effect against sulfonamide sensitive Gram-positive and Gram-negative microorganisms commonly isolated from secondary cutaneous pyogenic infections. It acts by restricting the synthesis of folic acid required by bacteria for growth, by its competition with para-aminobenzoic acid. There is no clinical data available on the degree and rate of systemic absorption of this product when applied to the skin or scalp. However, signiﬁcant absorption of sodium sulfacetamide through the skin has been reported.

The following in vitro data is available but the clinical signiﬁcance is unknown. Organisms that show susceptibility to sodium sulfacetamide are: Streptococci, Staphylococci, E. coli, Klebsiella pneumoniae, Pseudomonas pyocyanea, Salmonella species, Proteus vulgaris, Nocardia and Actinomyces. The exact mode of action of sulfur in the treatment of acne is unknown, but it has been reported that it inhibits the growth of Propionibacterium acnes and the formation of free fatty acids.

INDICATIONS

This product is indicated for use in the topical control of acne vulgaris, acne rosacea and seborrheic dermatitis.

CONTRAINDICATIONS

This product is contraindicated in persons with known or suspected hypersensitivity to sulfonamides, sulfur or any other ingredients of this product. This product is not to be used by patients with kidney disease.

WARNINGS

Sulfonamides are known to cause Stevens-Johnson syndrome in hypersensitive individuals. Stevens-Johnson syndrome also has been reported following the use of sodium sulfacetamide topically. Cases of drug-induced systemic lupus erythematosus from topical sulfacetamide also have been reported. In one of these cases, there was a fatal outcome.

KEEP OUT OF REACH OF CHILDREN.

PRECAUTIONS

FOR EXTERNAL USE ONLY. NOT FOR OPHTHALMIC USE. Avoid contact with eyes, lips and mucous membranes.

General

Nonsusceptible organisms, including fungi, may proliferate with the use of this preparation.

Although rare, sensitivity to sodium sulfacetamide may occur. Therefore, caution and careful supervision should be observed when prescribing this drug for patients who may be prone to hypersensitivity to topical sulfonamides. If the use of this product produces signs of hypersensitivity or other untoward reactions, discontinued use of the preparation. Patients should be carefully observed for possible local irritation or sensitization during long-term therapy. Systemic toxic reactions such as granulocytosis, acute hemolytic anemia, purpura hemorrhagica, drug fever, jaundice, and contact dermatitis indicate hypersensitivity to sulfonamides. Particular caution should be employed if areas of denuded or abraded skin are involved. Systemic absorption of topical sulfonamides is greater following application to large, infected, abraded, denuded or severely burned areas. Under these circumstances, any of the adverse effects produced by the systemic administration of these agents could potentially occur, and appropriate observations and laboratory determinations should be performed. The object of this therapy is to achieve desquamation without irritation, but sodium sulfacetamide and sulfur can cause reddening and scaling of the epidermis. These side effects are not unusual in the treatment of acne vulgaris, but patients should be cautioned about the possibility.

Information for Patients

Patients should discontinue the use of this product if the condition becomes worse or if a rash develops in the area being treated or elsewhere. The use of this product also should be discontinued promptly and the physician notiﬁed if any arthritis, fever or sores in the mouth develop. Avoid contact with eyes, eyelids, lips and mucous membranes.

Drug Interactions

This product is incompatible with silver preparations.

Carcinogenesis, Mutagenesis and Impairment of Fertility

Long-term animal studies for carcinogenic potential have not been performed on this product to date. Studies on reproduction and fertility also have not been performed. Chromosomal nondisjunction has been reported in the yeast, Saccharomyces cerevisiae, following application of sodium sulfacetamide. The signiﬁcance of this ﬁnding to the topical use of sodium sulfacetamide in the human is unknown.

Pregnancy

Category C

Animal reproduction studies have not been conducted with this product. It is also not known whether this product can affect reproduction capacity or cause fetal harm when administered to a pregnant woman. This product should be used by a pregnant woman only if clearly needed or when potential beneﬁts outweigh potential hazards to the fetus.

Nursing Mothers

It is not known whether this drug is excreted in the human milk. Because many drugs are excreted in human milk, caution should be exercised when this product is administered to a nursing woman.

Pediatric Use

Safety and effectiveness in children under the age of 12 have not been established.

DOSAGE AND ADMINISTRATION

Wash affected areas once or twice daily, or as directed by your physician. Wet skin and liberally apply to areas to be cleansed. Massage gently into skin for 10 to 20 seconds working into a full lather, rinse thoroughly and pat dry. If skin dryness occurs, it may be controlled by rinsing cleanser off sooner or using less frequently.

See booklet for full prescribing information.

STORAGE

Store at 20°C to 25°C (68°F to 77°F), excursions permitted between 15°C and 30°C (between 59°F and 86°F). Protect from freezing and excessive heat. Keep bottle tightly closed.

To report a serious adverse event or obtain product information, please contact Westminster Pharmaceuticals at 1-844-221-7294.

Manufactured for:
Westminster Pharmaceuticals, LLC
Nashville, TN 37217

Rev. 12/22

PRINCIPAL DISPLAY PANEL - 285 g Bottle Label

NDC 69367-244-10
Rx Only

Sodium
Sulfacetamide 9.8%
and Sulfur 4.8%
Cleanser

For External Use Only

Net Wt. 10 oz
(285 g)

Westminster
Pharmaceuticals